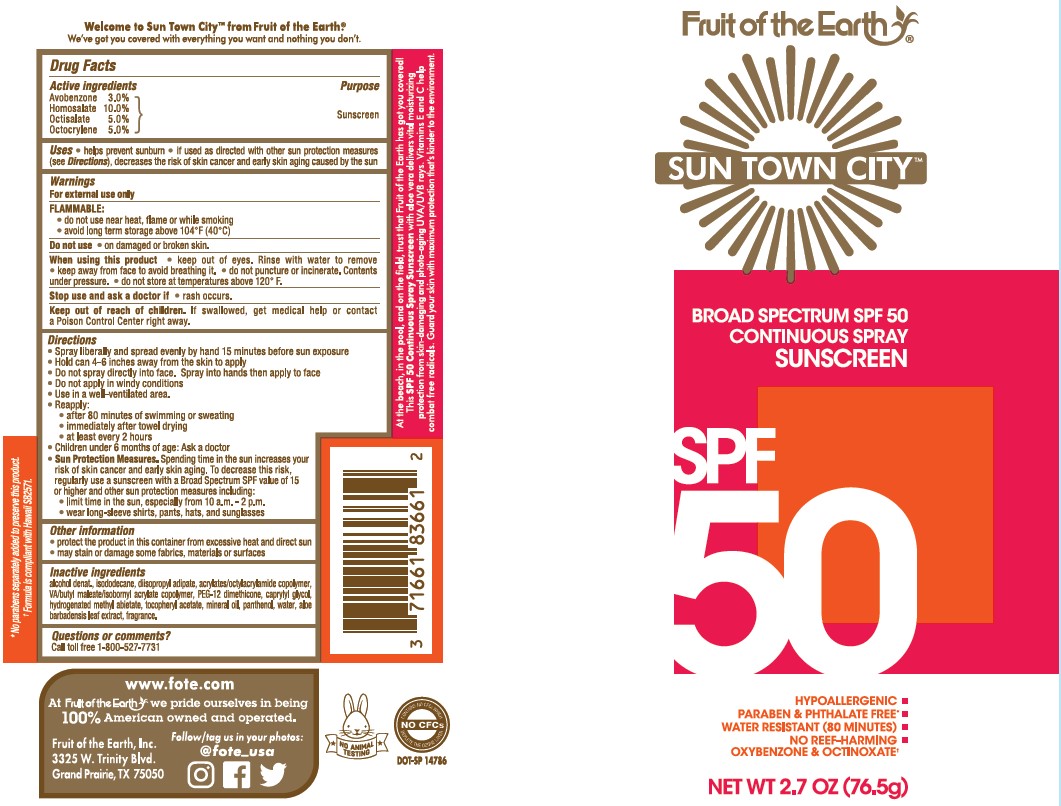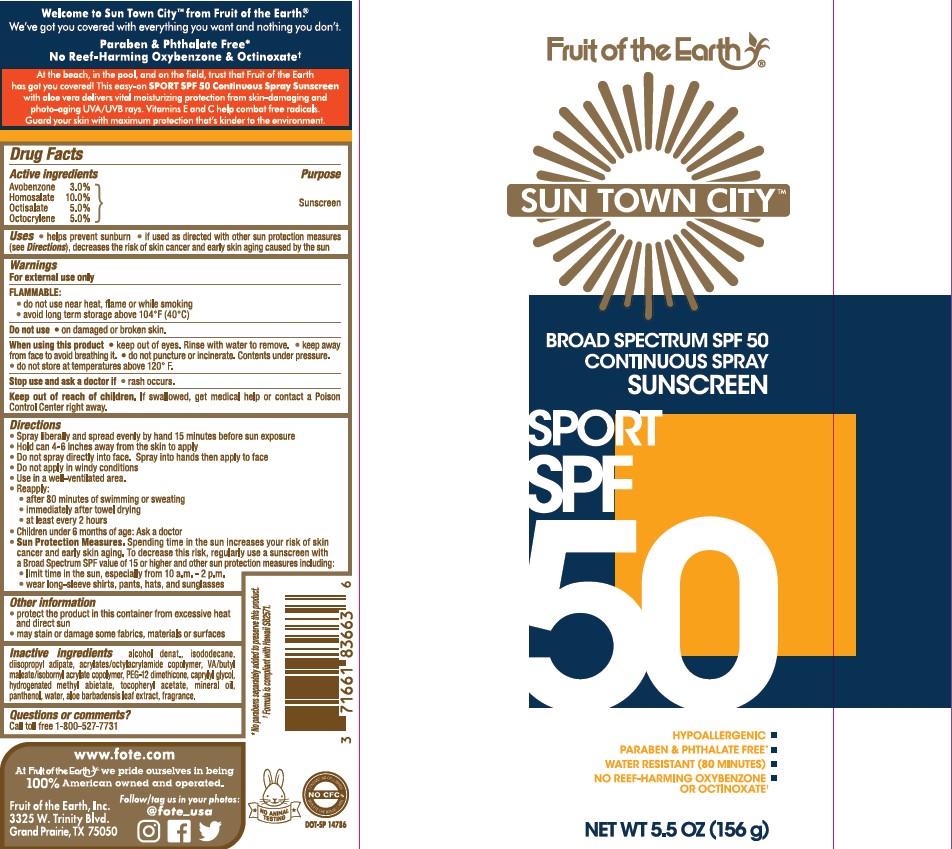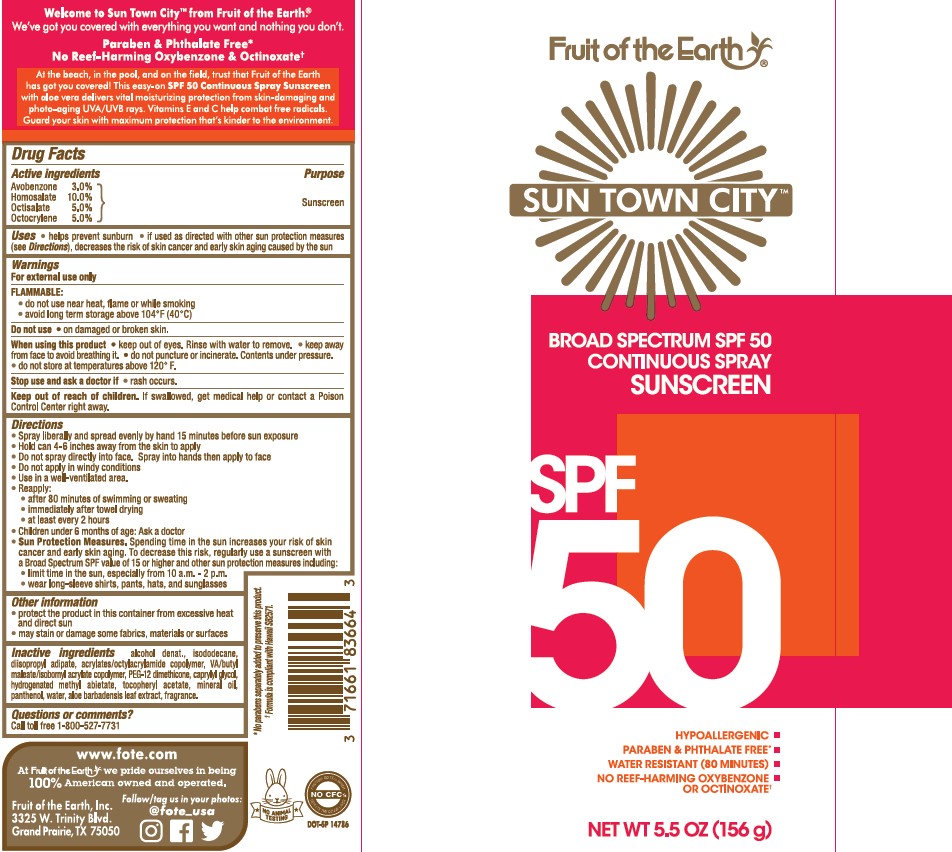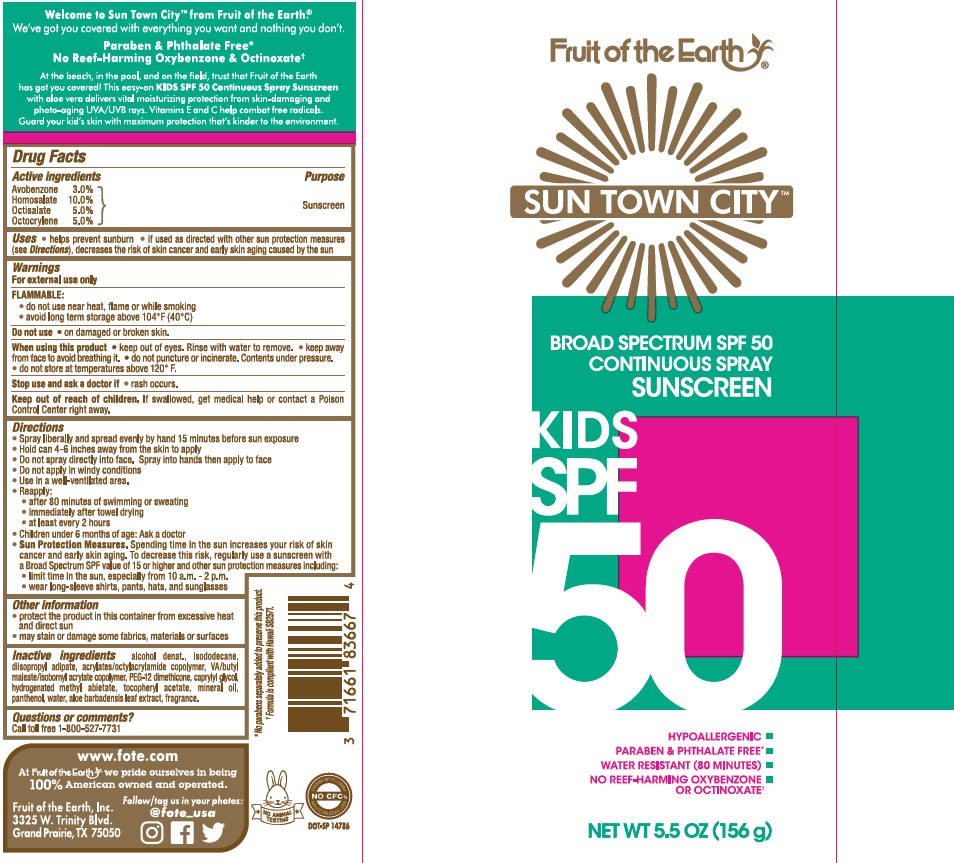 DRUG LABEL: Fruit of The Earth Sun Town City Kids SPF 50 Sunscreen
NDC: 62217-067 | Form: SPRAY
Manufacturer: Fruit of the Earth, Inc.
Category: otc | Type: HUMAN OTC DRUG LABEL
Date: 20241017

ACTIVE INGREDIENTS: AVOBENZONE 30 mg/1 g; HOMOSALATE 100 mg/1 g; OCTISALATE 50 mg/1 g; OCTOCRYLENE 50 mg/1 g
INACTIVE INGREDIENTS: ASCORBYL PALMITATE; ALCOHOL; ACRYLATE/ISOBUTYL METHACRYLATE/N-TERT-OCTYLACRYLAMIDE COPOLYMER (75000 MW); ISODODECANE; DIISOPROPYL ADIPATE; PEG-12 DIMETHICONE; CAPRYLYL GLYCOL; .ALPHA.-TOCOPHEROL ACETATE; METHYL HYDROGENATED ROSINATE; MINERAL OIL; PANTHENOL; WATER; ALOE VERA LEAF

Fruit of The Earth Sun Town City Kids SPF 50 Continuous Spray Sunscreen

Active Ingredients

Avobenzone 3.0%, Homosalate 10.0%, Octisalate 5.0%, Octocrylene 5.0%

Purpose

Sunscreen

Uses

• helps prevent sunburn • if used as directed with other sun protectino measures (see Directions), decreases the risk of skin cancer and early skin aging caused by the sun

Warnings

For external use only

Flammable:

- do not use near heat, flame or while smoking
- avoid long term storage above 104°F (40°C)

Do not use

• on damaged or broken skin.

When using this product

• keep out of eyes. Rinse with water to remove • keep away from face to avoid breathing it. • do not puncture or incerate. Contents under pressures. • do not store at temperatures above 120°F.

Stop use and ask a doctor if

• if rash occurs.

Keep out of reach of children.

If swallowed, get medical help or contact a Poison Control Center right away.

Directions

- Spray liberally and spread evenly by hand 15 minutes before sun exposure
- Hold can 4-6 inches away from the skin to apply
- Do not spray directly into face. Spray into hands then apply to face
- Do not apply in windy conditions
- Use in a well-ventilated area.
- Reapply:

• after 80 minutes of swimming or sweating

• immediately after towel drying

• at least every 2 hours

- Children under 6 months of age: Ask a doctor
- Sun protection measures. Spending time in the sun increases your risk of skin cancer and early skin aging. To decrease this risk, regularly use a sunscreen with a Broad Spectrum SPF value of 15 or higher and othe rsun protection measures including:

• limit time in the sun, especially from 10 a.m. - 2 p.m.

• wear long-sleeved shirts, pants, hats, and sunglasses

Other Information

- protect the product in this container from excessive heat and direct sun
- may stain or damage some fabrics, materials or surfaces

Inactive Ingredients

alcohol denat., isododecane, diisopropyl adipate, acrylates/octylacrylamide copolymer, VA/butyl maleate/isobornyl acrylate copolymer, PEG-12 dimethicone, caprylyl glycol, hydrogenated methyl abietate, tocopheryl acetate, mineral oil, panthenol, water, aloe barbadensis leaf extract, fragrance.